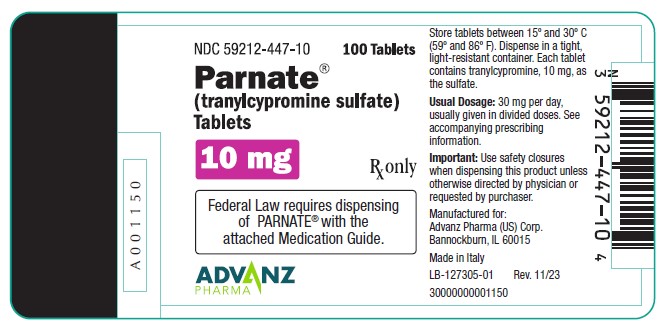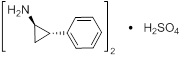 DRUG LABEL: PARNATE
NDC: 59212-447 | Form: TABLET, FILM COATED
Manufacturer: Advanz Pharma (US) Corp.
Category: prescription | Type: Human Prescription Drug Label
Date: 20250702

ACTIVE INGREDIENTS: TRANYLCYPROMINE SULFATE 10 mg/1 1
INACTIVE INGREDIENTS: CELLULOSE, MICROCRYSTALLINE; ANHYDROUS CITRIC ACID; CROSCARMELLOSE SODIUM; D&C RED NO. 7; FD&C BLUE NO. 2; FD&C YELLOW NO. 6; GELATIN; LACTOSE; MAGNESIUM STEARATE; TALC; TITANIUM DIOXIDE; CARNAUBA WAX; POLYETHYLENE GLYCOL 400; POLYETHYLENE GLYCOL 8000; HYPROMELLOSE 2910 (6 MPA.S)

HIGHLIGHTS OF PRESCRIBING INFORMATION

These highlights do not include all the information needed to use PARNATE safely and effectively. See full prescribing information for PARNATE.
Parnate® (tranylcypromine) tablets, for oral use
Initial U.S. Approval: 1961

WARNING: SUICIDAL THOUGHTS AND BEHAVIORS and HYPERTENSIVE CRISIS WITH SIGNIFICANT TYRAMINE USE

See full prescribing information for complete boxed warning.

- Increased risk of suicidal thoughts and behavior in pediatric and young adult patients taking antidepressants. Closely monitor all antidepressant-treated patients for clinical worsening and emergence of suicidal thoughts and behaviors. PARNATE is not approved for use in pediatric patients. (5.1, 8.4)
- Excessive consumption of foods or beverages with significant tyramine content or certain drugs can precipitate hypertensive crisis. Monitor blood pressure, allow for medication free intervals, and advise patients to avoid foods and beverages with high tyramine content. (5.2, 7.1, 7.2)

1 INDICATIONS AND USAGE

- PARNATE is a monoamine oxidase inhibitor (MAOI) indicated for the treatment of major depressive disorder (MDD) in adult patients who have not responded adequately to other antidepressants (1)
- PARNATE is not indicated for the initial treatment of MDD due to the potential for serious adverse reactions and drug interactions, and the need for dietary restrictions (1, 4,5,7)

2 DOSAGE AND ADMINISTRATION

- Recommended daily dosage is 30 mg in divided doses (2.1)
- If no adequate response, increase dosage in increments of 10 mg per day every 1 to 3 weeks to a maximum dosage of 30 mg twice daily (60 mg per day). Consider more gradual dosage increases in patients at risk for hypotension (2.1)
- Consider discontinuing PARNATE therapy gradually because of the risk for withdrawal effects (2.3,5.8,9.3)
- Switching from or to other MAOIs or other antidepressants: See full prescribing information for instructions (2.2,7.1)

3 DOSAGE FORMS AND STRENGTHS

Tablets: 10 mg (3)

4 CONTRAINDICATIONS

- Concomitant use or use in rapid succession with other MAOIs; selective serotonin reuptake inhibitors; serotonin and norepinephrine reuptake inhibitors; tricyclic antidepressants; sympathomimetic drugs; and numerous other drugs. See Full Prescribing Information for the full list of contraindicated products (4.1, 7.1)
- Pheochromocytoma, other catecholamine-releasing paraganglioma (4.2)

5 WARNINGS AND PRECAUTIONS

- Activation of Mania/Hypomania: May be precipitated by antidepressant treatment in patients with bipolar disorder.Screen patients prior to treatment (5.4)
- Hypotension (including syncope): Monitor patients and adjust PARNATE dosage or concomitant medication as necessary (5.5)
- Hypotension and Hypertension during Anesthesia and Perioperative Care: If possible, discontinue PARNATE prior to elective surgery (5.6)
- Hepatitis and Elevated Liver Enzymes: Monitor accordingly (5.10)

6 ADVERSE REACTIONS

Most common adverse reactions (>10%) were dry mouth, dizziness, insomnia, sedation, headache, overexcitement, constipation, blurred vision, and tremor (6)

To report SUSPECTED ADVERSE REACTIONS, contact Advanz Pharma (US) Corp. at 1-877-370-1142 or FDA at 1-800-FDA-1088 or www.fda.gov/medwatch.

7 DRUG INTERACTIONS

See Full Prescribing Information for a list of products, foods and beverages that can interact with PARNATE. (7)

FULL PRESCRIBING INFORMATION

WARNING: SUICIDAL THOUGHTS AND BEHAVIORS and HYPERTENSIVE CRISIS WITH SIGNIFICANT TYRAMINE USE

Suicidal Thoughts and Behaviors
Antidepressants increased the risk of suicidal thoughts and behaviors in pediatric and young adult patients in short-term studies. Closely monitor all antidepressant-treated patients for clinical worsening, and for emergence of suicidal thoughts and behaviors [see Warnings and Precautions (5.1)]. PARNATE is not approved for use in pediatric patients [see Use in Specific Populations (8.4)].
Hypertensive Crisis with Significant Tyramine Use
Excessive consumption of foods or beverages with significant tyramine content or the use of certain drugs with PARNATE or after PARNATE discontinuation can precipitate hypertensive crisis. Monitor blood pressure and allow for medication-free intervals between administration of PARNATE and interacting drugs. Instruct patients to avoid ingestion of foods and beverages with high tyramine content [see Warnings and Precautions (5.2) and Drug Interactions(7.1, 7.2)].

1 INDICATIONS AND USAGE

PARNATE is indicated for the treatment of major depressive disorder (MDD) in adult patients who have not responded adequately to other antidepressants. PARNATE is not indicated for the initial treatment of MDD due to the potential for serious adverse reactions and drug interactions, and the need for dietary restrictions [see Contraindications (4), Warnings and Precautions (5), and Drug Interactions (7)].

2 DOSAGE AND ADMINISTRATION

2.1 Recommended Dosage

PARNATE tablets are for oral use. The recommended dosage is 30 mg per day (in divided doses). If patients do not have an adequate response, increase the dosage in increments of 10 mg per day every 1 to 3 weeks to a maximum 30 mg twice daily (60 mg per day). Dosage increases should be made more gradually in patients at risk for hypotension (e.g., geriatric patients) [see Warnings and Precautions (5.5)].

2.2 Switching to or from Other Antidepressants

Switching from Contraindicated Antidepressants to PARNATE
After stopping treatment with contraindicated antidepressants, a time period of 4 to 5 half-lives of the other antidepressant or any active metabolite should elapse before starting treatment with PARNATE. After stopping treatment with an MAO inhibitor antidepressant, a time period of at least one week or 4 to 5 half-lives of the other MAO inhibitor (whichever is longer) should elapse before starting treatment with PARNATE to reduce the risk of additive effects [see Contraindications (4.1) and Drug Interactions (7.1)].
Switching from PARNATE to Other MAOIs or Contraindicated Antidepressants
After stopping PARNATE treatment, at least one week should elapse before starting another MAOI (intended to treat MDD) or other contraindicated antidepressants. Refer to the prescribing information of the subsequently used drug for product-specific advice on a medication-free interval [see Contraindications (4.1) and Drug Interactions (7.1)].

2.3 Discontinuing Treatment

Withdrawal effects, including delirium, have been reported with abrupt discontinuation of PARNATE therapy. Higher daily doses and longer duration of use appear to be associated with a higher risk of withdrawal effects. Consider discontinuing PARNATE therapy by slow, gradual dosage reduction [see Warnings and Precautions (5.8) and Drug Abuse and Dependence (9.3)].

2.4 Screen for Bipolar Disorder and Elevated Blood Pressure Prior to Starting PARNATE

Prior to initiating treatment with PARNATE:

- Screen patients for a history of mania [see Warnings and Precautions (5.4)].
- Measure blood pressure[see Warnings and Precautions (5.2, 5.5)].

3 DOSAGE FORMS AND STRENGTHS

Tablets containing tranylcypromine sulfate equivalent to 10 mg tranylcypromine are round, rose‑red, film‑coated, and debossed on one side with “PARNATE” and “SB.”

4 CONTRAINDICATIONS

4.1 Combination with Certain Drugs

Concomitant use of PARNATE or use in rapid succession with the products in Table 1 is contraindicated. Such use may cause severe or life-threatening reactions such as hypertensive crises or serotonin syndrome [see Drug Interactions (7.1)]. Medication-free periods between administration of PARNATE and contraindicated agents are recommended [see Dosage and Administration (2.2) and Drug Interactions (7.1)].
Table 1: Products Contraindicated with the Use of PARNATE

Drug Classes
Non-selective H1 receptor antagonists
Antidepressants including but not limited to:
- Other monoamine oxidase inhibitors (MAOIs)
- Selective serotonin reuptake inhibitors (SSRIs) and serotonin and norepinephrine reuptake inhibitors (SNRIs)
- Tricyclic antidepressants
- Other antidepressants (e.g., amoxapine, bupropion, maprotiline, nefazodone, trazodone, vilazodone, vortioxetine)
Amphetamines and methylphenidates and derivatives
Sympathomimetic products (e.g., cold, hay fever or weight reducing products that contain vasoconstrictors such as pseudoephedrine, phenylephrine, and ephedrine; or dietary supplements that contain sympathomimetics)
Triptans
Individual Drugs (not included in the above classes)
buspirone | levodopa | s-adenosyl-L-methionine (SAM-e)
carbamazepine | meperidine | tapentadol
cyclobenzaprine | methyldopa | tetrabenazine
dextromethorphan | milnacipran | tryptophan
dopamine | rasagiline
hydroxytryptophan | reserpine

4.2 Pheochromocytoma and Catecholamine-Releasing Paragangliomas

PARNATE is contraindicated in the presence of pheochromocytoma or other catecholamine-releasing paragangliomas because such tumors secrete pressor substances and can lead to hypertensive crisis [see Warnings and Precautions (5.3)].

5 WARNINGS AND PRECAUTIONS

5.1 Suicidal Thoughts and Behaviors in Adolescents and Young Adults

In pooled analyses of placebo-controlled trials of antidepressant drugs (SSRIs and other antidepressant classes) that included approximately 77,000 adult patients and 4,500 pediatric patients, the incidence of suicidal thoughts and behaviors in antidepressant-treated patients age 24 years and younger was greater than in placebo-treated patients. There was considerable variation in risk of suicidal thoughts and behaviors among drugs, but there was an increased risk identified in young patients for most drugs studied. There were differences in absolute risk of suicidal thoughts and behaviors across the different indications, with the highest incidence in patients with MDD. The drug-placebo differences in the number of cases of suicidal thoughts and behaviors per 1000 patients treated are provided in Table 2.

Table 2: Risk Differences of the Number of Patients of Suicidal Thoughts and Behavior in the Pooled Placebo-Controlled Trials of Antidepressants in Pediatric and Adult Patients

Age Range | Drug-Placebo Difference in Number of Patients of Suicidal Thoughts or Behaviors per 1000 Patients Treated
 | Increases Compared to Placebo
<18 years old | 14 additional patients
18-24 years old | 5 additional patients
 | Decreases Compared to Placebo
25-64 years old | 1 fewer patient
≥65 years old | 6 fewer patients

It is unknown whether the risk of suicidal thoughts and behaviors in children, adolescents, and young adults extends to longer-term use, i.e., beyond four months. However, there is substantial evidence from placebo-controlled maintenance trials in adults with MDD that antidepressants delay the recurrence of depression and that depression itself is a risk factor for suicidal thoughts and behaviors.

Monitor all antidepressant-treated patients for any indication for clinical worsening and emergence of suicidal thoughts and behaviors, especially during the initial few months of drug therapy, and at times of dosage changes. Counsel family members or caregivers of patients to monitor for changes in behavior and to alert the healthcare provider. Consider changing the therapeutic regimen, including possibly discontinuing PARNATE, in patients whose depression is persistently worse, or who are experiencing emergent suicidal thoughts or behaviors.

5.2 Hypertensive Crisis and Hypertension

Hypertensive Crisis
MAOIs, including PARNATE, have been associated with hypertensive crises caused by the ingestion of foods or beverages with a high concentration of tyramine. In addition, hypertensive reactions and crises may occur with concomitant use of other drugs [see Drug Interactions (7.1)]. Patients with hyperthyroidism may be at greater risk of hypertensive crisis.
Signs, Symptoms, and Complications of Hypertensive Crisis: In some patients a hypertensive crisis constitutes a hypertensive emergency, which requires immediate attention to prevent serious complications or fatal outcome. These emergencies are characterized by severe hypertension (e.g., with a blood pressure of more than 180/120 mm Hg) and evidence of organ dysfunction. Symptoms may include occipital headache (which may radiate frontally), palpitations, neck stiffness or soreness, nausea or vomiting, sweating (sometimes with fever or cold, clammy skin), dilated pupils, photophobia, shortness of breath, or confusion. Either tachycardia or bradycardia may be present and may be associated with constricting chest pain. Seizures may also occur. Intracranial bleeding, sometimes fatal, has been reported in association with the increase in blood pressure.
Strategies to Reduce the Risk of Hypertensive Crisis: Instruct patients to avoid foods and beverages with high tyramine content while being treated with PARNATE and for 2 weeks after stopping PARNATE [see Drug Interactions (7.2)]. Careful evaluation of the benefits and risks of PARNATE therapy is necessary in patients with:

- Hypertension or confirmed or suspected cerebrovascular or cardiovascular disorders that constitute an increased risk for complications from severe hypertension, and
- A history of headaches that can mask the occurrence of headaches as prodromal of a hypertensive crisis.

In all patients taking PARNATE, monitor blood pressure closely to detect evidence of increased blood pressure. Full reliance should not be placed on blood pressure readings. The patient should also be observed for other signs and symptoms of hypertensive crisis.
Treatment of Hypertensive Crisis: Therapy should be interrupted with symptoms that may be prodromal or a manifestation of a hypertensive crisis, such as palpitations or headaches, and patients should be evaluated immediately. Discontinue PARNATE, other drugs, foods or beverages suspected to contribute to the hypertensive crisis immediately [see Drug Interactions (7.1, 7.2)].
Patients with severe elevations in blood pressure (e.g., more than 180/120 mm Hg) with evidence of organ dysfunction require immediate blood pressure reduction. Fever should be managed by means of external cooling. However, additional measures to control the causes of hyperthermia (psychomotor agitation, increased neuromuscular activity, persistent seizures) may be required.
Hypertension
Clinically significant increases in blood pressure have also been reported after the administration of MAOIs, including PARNATE, in patients not ingesting tyramine-rich foods or beverages. Assess blood pressure before prescribing PARNATE and closely monitor blood pressure in all patients taking PARNATE.

5.3 Serotonin Syndrome

The development of a potentially life-threatening serotonin syndrome has been reported with MAOIs when used concomitantly with other serotonergic drugs. Such drugs include SSRIs, SNRIs, tricyclic antidepressants, triptans, fentanyl, lithium, tramadol, tryptophan, buspirone, St. John’s wort, S-adenosyl-L-methionine (SAM-e), and other MAOIs used to treat nonpsychiatric disorders (such as linezolid or intravenous methylene blue).

Manifestations of the serotonin syndrome may include mental status changes (e.g., agitation, hallucinations, delirium, coma), autonomic instability (e.g., tachycardia, labile blood pressure, dizziness, diaphoresis, flushing, hyperthermia; with possible rapid fluctuations of vital signs), neuromuscular symptoms (e.g., tremor, rigidity, myoclonus, hyper-reflexia, incoordination), seizures, and/or gastrointestinal symptoms (e.g., nausea, vomiting, diarrhea). Fatal outcome of serotonin syndrome has been reported, including in patients who had been treated with PARNATE. In some cases of an interaction between PARNATE and SSRIs or SNRIs, the features of the syndrome resembled neuroleptic malignant syndrome.

The concomitant use, or use in rapid succession, of PARNATE with other serotonergic drugs is contraindicated. However, there may be circumstances when treatment with other serotonergic substances (such as linezolid or intravenous methylene blue) is necessary and cannot be delayed. In such cases, PARNATE must be discontinued as soon as possible before initiating treatment with the other agent.

Treatment with PARNATE and any concomitant serotonergic agents should be discontinued immediately if the above events occur, and supportive symptomatic treatment should be initiated.

5.4 Activation of Mania/Hypomania

In patients with bipolar disorder, treating a depressive episode with PARNATE or another antidepressant may precipitate a mixed/manic episode. Prior to initiating treatment with PARNATE, screen patients for any personal or family history of bipolar disorder, mania, or hypomania.

5.5 Hypotension

Hypotension, including postural hypotension, has been observed during therapy with PARNATE. At doses above 30 mg daily, postural hypotension is a major adverse reaction and may result in syncope. Symptoms of postural hypotension are seen most commonly, but not exclusively, in patients with pre-existing hypertension. Blood pressure usually returns rapidly to pretreatment levels upon discontinuation of PARNATE.
Dosage increases should be made more gradually in patients with a tendency toward hypotension and/or postural hypotension (e.g., elderly patients) [see Dosage and Administration (2.2) and Use in Specific Populations (8.5)]. Such patients should be closely observed for postural changes in blood pressure throughout treatment. Also, when PARNATE is used concomitantly with other agents known to cause hypotension, the possibility of additive hypotensive effects should be considered [see Drug Interactions (7.1)]. Postural hypotension may be relieved by having patients lie down until blood pressure returns to normal.

5.6 Hypotension and Hypertension during Anesthesia and Perioperative Care

It is recommended that PARNATE be discontinued at least 10 days prior to elective surgery. If this is not possible, for general anesthesia, regional and local anesthesia, and perioperative care avoid the use of agents that are contraindicated for concomitant use with PARNATE. Carefully consider the risk of agents and techniques that increase the risk for hypotension (e.g., epidural or spinal anesthesia) or other adverse reactions to PARNATE (e.g., hypertension associated with the use of vasoconstrictors in local anesthetics).

5.7 Need for Emergency Treatment with Contraindicated Drugs

If in the absence of therapeutic alternatives emergency treatment with a contraindicated product (e.g., linezolid, intravenous methylene blue, direct-acting sympathomimetic drugs such as epinephrine) becomes necessary and cannot be delayed, discontinue PARNATE as soon as possible before initiating treatment with the other product and monitor closely for adverse reactions [see Drug Interactions (7.1)]

5.8 Discontinuation Syndrome

Abrupt discontinuation or dosage reduction of PARNATE has been associated with the appearance of new symptoms that include dizziness, nausea, headache, irritability, insomnia, diarrhea, anxiety, fatigue, abnormal dreams, and hyperhidrosis. In general, discontinuation events occurred more frequently with longer duration of therapy.

There have been spontaneous reports of adverse reactions occurring upon discontinuation of MAOIs, particularly when abrupt, including dysphoric mood, irritability, agitation, dizziness, sensory disturbances (e.g. paresthesia, such as electric shock sensations), anxiety, confusion, headache, lethargy, emotional lability, insomnia, hypomania, tinnitus, and seizures. While these reactions are generally self-limiting, there have been reports of prolonged discontinuation symptoms.

Patients should be monitored for these symptoms when discontinuing treatment with PARNATE. A gradual reduction in the dose rather than abrupt cessation is recommended whenever possible [see Dosage and Administration (2.3) and Adverse Reactions (6)].

5.9 Risk of Clinically Significant Adverse Reactions due to Persistence of MAO Inhibition after Discontinuation

Although excretion of PARNATE is rapid, inhibition of MAO may persist up to 10 days following discontinuation. This should be taken into account when considering the use of potentially interacting substances or the consumption of tyramine-rich food or beverages [see Drug Interactions (7.2)], or when interpreting adverse reactions observed after discontinuation of PARNATE. Care should be taken to differentiate symptoms of persistent MAO inhibition from withdrawal symptoms [see Drug Abuse and Dependence (9.3)].

5.10 Hepatotoxicity

Hepatitis and elevated aminotransferases have been reported in association with PARNATE administration. Patients should be monitored accordingly. PARNATE should be discontinued in patients who develop signs and symptoms of hepatotoxicity.

Sedation has occurred in PARNATE-treated patients with cirrhosis. Patients with cirrhosis receiving PARNATE should be monitored for possible increased risks of central nervous system adverse reactions, such as excessive drowsiness.

5.11 Seizures

Seizures have been reported with PARNATE withdrawal after abuse, and with overdose. Patients at risk for seizures should be monitored accordingly.

5.12 Hypoglycemia in Diabetic Patients

Some MAOIs have contributed to hypoglycemic episodes in diabetic patients receiving insulin or other blood-glucose-lowering agents. Monitor blood glucose in patients receiving both PARNATE and blood-glucose-lowering agents. A reduction of the dosage of such agents may be necessary [see Drug Interactions (7.1)]

5.13 Aggravation of Coexisting Symptoms of Depression

PARNATE may aggravate coexisting symptoms in depression, such as anxiety and agitation.

5.14 Adverse Effects on the Ability to Drive and Operate Machinery

Some PARNATE adverse reactions (e.g., hypotension, faintness, drowsiness, confusion, disorientation) can impair a patient’s ability to operate machinery or use an automobile. Patients should be cautioned about operating hazardous machinery, including automobiles, until they are reasonably certain that PARNATE therapy does not impair their ability to engage in such activities.

6 ADVERSE REACTIONS

The following adverse reactions are described in greater detail in other sections:

- Suicidal thoughts and behaviors [see Warnings and Precautions (5.1)]
- Hypertensive crisis and hypertension [see Warnings and Precautions (5.2)]
- Serotonin syndrome [see Warnings and Precautions (5.3)]
- Activation of mania/hypomania [see Warnings and Precautions (5.4)]
- Hypotension [see Warnings and Precautions (5.5)]
- Hypotension and hypertension during anesthesia and perioperative care [see Warnings and Precautions (5.6)]
- Discontinuation syndrome [ see Warnings and Precautions (5.8)]
- Persistence of MAO inhibition after discontinuation [see Warnings and Precautions (5.9)]
- Hepatotoxicity [see Warnings and Precautions (5.10)]
- Seizures[see Warnings and Precautions (5.11)]
- Hypoglycemia in diabetic patients [see Warnings and Precautions (5.12)]
- Aggravation of coexisting symptoms of depression [see Warnings and Precautions (5.13)]
- Adverse effects on the ability to drive and operate machinery [see Warnings and Precautions (5.14)]

Because clinical trials are conducted under widely varying conditions, adverse reaction rates observed in the clinical trials of a drug cannot be directly compared to rates in the clinical trials of another drug and may not reflect the rates observed in practice.
Based on clinical trial data, the most common adverse reactions to tranylcypromine were dry mouth, dizziness, insomnia, sedation, and headache (>30%) and overexcitement, constipation, blurred vision, and tremor (>10%).
The following adverse reactions have been identified in clinical trials or during postapproval use of PARNATE:
Blood and lymphatic system disorders: agranulocytosis, leukopenia, thrombocytopenia, anemia
Endocrine disorders: impaired water excretion compatible with the syndrome of inappropriate secretion of antidiuretic hormone (SIADH)
Metabolism and nutrition disorders: significant anorexia, weight gain
Psychiatric disorders: excessive stimulation/overexcitement, manic symptoms/hypomania, agitation, insomnia, anxiety, confusion, disorientation, loss of libido
Nervous system disorders: dizziness, restlessness/akathisia, akinesia, ataxia, myoclonic jerks, tremor, hyper-reflexia, muscle spasm, paresthesia, numbness, memory loss, sedation, drowsiness, dysgeusia, headaches (without blood pressure elevation)
Eye disorders: blurred vision, nystagmus
Ear and labyrinth disorders: tinnitus
Cardiac disorders: tachycardia, palpitations
Vascular disorders: hypertensive crisis, hypertension, hypotension (including postural hypotension with syncope)
Gastrointestinal disorders: diarrhea, constipation, nausea, abdominal pain, dry mouth, fissuring in corner of mouth
Hepatobiliary disorders: hepatitis, elevated aminotransferases
Skin and subcutaneous tissue disorders: localized scleroderma, flare-up of cystic acne, urticaria, rash, alopecia, sweating
Renal and urinary disorders: urinary retention, urinary incontinence, urinary frequency
Reproductive system and breast disorders: impotence, delayed ejaculation
General disorders and administration site conditions: edema, chills, weakness, fatigue/lethargy

7 DRUG INTERACTIONS

7.1 Clinically Significant Drug Interactions

Tables 3 and 4 lists drug classes and individual products, respectively, with a potential for interaction with PARNATE, describes the predominant observed or anticipated risks, and provides advice on concomitant use. Given serious adverse reactions with multiple agents, patients should avoid taking over-the-counter medications or dietary supplements without prior consultation with a healthcare provider able to provide advice on the potential for interactions.

Time to Start PARNATE after Discontinuation of a Contraindicated Drug

For products that are contraindicated with PARNATE, a time period of 4 to 5 half-lives of the other product or any active metabolite should elapse before starting treatment with PARNATE. After stopping treatment with an MAO inhibitor antidepressant, a time period of at least 1 week or 4 to 5 half-lives of the other MAO inhibitor (whichever is longer) should elapse before starting treatment with PARNATE because of the risk for clinically significant adverse reactions after discontinuation due to persistent MAO inhibition [see Dosage and Administration (2.2), Warnings and Precautions (5.9) ]. This period can be several weeks long (e.g., a minimum of 5 weeks for fluoxetine given fluoxetine's long half-life). Refer to the prescribing information of the contraindicated product for relevant information.

Time to Start Contraindicated Drug after Discontinuation of PARNATE
The potential for interactions persists after discontinuation of PARNATE until MAO activity has sufficiently recovered. Inhibition of MAO may persist up to 10 days following discontinuation [see Warnings and Precautions (5.9)]. After stopping PARNATE, at least 1 week should elapse before starting another MAOI (intended to treat MDD) or other contraindicated antidepressants. Refer to the prescribing information of any agent considered for subsequent use for recommendations on the duration of a waiting period after discontinuation of a MAO inhibitor.

If in the absence of therapeutic alternatives and emergency treatment with a contraindicated drug (e.g., linezolid, intravenous methylene blue, direct-acting sympathomimetic drugs such as epinephrine) becomes necessary and cannot be delayed, discontinue PARNATE as soon as possible before initiating treatment with the other agent, and monitor closely for adverse reactions.

Table 3 Clinically Significant Drug Interactions with Drug Classes*

Product | Clinical Comment on Concomitant Usea | Predominant Effect/Risk [Hypertensive Reaction (HR)b or Serotonin Syndrome (SS)c]
Agents with blood pressure-reducing effects | Use with cautiond | Hypotensione
Non-selective H1 receptor antagonists | Contraindicateda | Increased anticholinergic effects
Beta-adrenergic blockers (see also agents or procedures with blood pressure-reducing effects) | Use with the cautiond | More pronounced bradycardia, postural hypotensione
Blood glucose-lowering agents | Dosage reduction of such agents may be necessary. Monitor blood glucose. | Excessive reduction of blood glucose (additive effect)f
CNS depressant agents (including opioids, alcohol, sedatives, hypnotics) | Use with cautiond | Increased CNS depression
Dietary supplements containing sympathomimetics | Contraindicateda
Antidepressants including but not limited to:; - Other MAOIs (e.g., linezolid, intravenous methylene blue, selective MAOIs) - Selective serotonin reuptake inhibitors (SSRIs) and serotonin and norepinephrine reuptake inhibitors (SNRIs) - Tricyclic antidepressants - Amoxapine, bupropion, maprotiline, nefazodone, trazodone, vilazodone, vortioxetine | Contraindicateda | SS for all antidepressants For MAOIs, increased MAO inhibition and risk of adverse reactions, SS, and HRg
Amphetamines and methylphenidates and derivatives | Contraindicateda | HR
Sympathomimetic drugs** | Contraindicateda | HR; Including risk of intracerebral hemorrhage
Triptans | Contraindicateda | SS

* Some drugs in these groups may also be listed in Table 4 below.
** Sympathomimetic drugs include amphetamines as well as cold, hay fever or weight-reducing products that contain vasoconstrictors such as pseudoephedrine, phenylephrine, and ephedrine)
a [See Contraindications (4.1)]; b [See Warnings and Precautions (5.2)]; c [See Warnings and Precautions (5.3)]
d If not otherwise specified in this table, consider avoiding concomitant use (see also information on medication-free intervals, use agent at the lowest appropriate dosage, monitor for effects of the interaction, advise the patient to report potential effects).
e [See Warnings and Precautions (5.5)]; f [See Warnings and Precautions (5.14)]; g [See Overdosage (10.1)]
Table 4: Clinically Significant Drug Interactions with Individual Products*

Product | Clinical Comment on Concomitant Usea | Predominant Effect/Risk [Hypertensive Reaction (HR)b or Serotonin Syndrome (SS)c]
Altretamine | Use with cautiond | Orthostatic hypotensione
Buspirone | Contraindicateda | HR
Carbamazepine | Contraindicateda | SS
Chlorpromazine | Use with cautiond | Hypotensive effectse
Cyclobenzaprine | Contraindicateda | SS
Dextromethorphan | Contraindicateda | SS; Psychosis, bizarre behavior
Dopamine | Contraindicateda | HR
Droperidol | Use with cautiond | QT interval prolongation
Entacapone | Use with cautiond | HR
Fentanyl | Use with cautiond | SS
Hydroxytryptophan | Contraindicateda | SS
Levodopa | Contraindicateda | HR
Lithium | Use with cautiond | SS
Meperidine | Contraindicateda | SS
Methadone | Use with cautiond | SS
Methyldopa | Contraindicateda | HR
Metoclopramide | Use with cautiond | HR/SS
Mirtazapine | Contraindicateda | SS
Oxcarbazepine | Use with cautiond because of close structural relationship with tricyclic antidepressants | SS
Rasagiline | Contraindicateda | HR
Reserpine | Contraindicateda | HR
S-adenosyl-L-methionine (SAM-e) | Contraindicateda | SS
Tapentadol | Contraindicateda | HR/SS
Tetrabenazine | Contraindicateda | HR
Tolcapone | Use with cautiond | HR
Tramadol | Use with cautiond | SS; Increased seizure risk
Tryptophan | Contraindicateda | SS

*Some drugs in this table may also belong to groups listed in Table 3 above, and may be associated with additional interactions.
a [See Contraindications (4.1)]; b [See Warnings and Precautions (5.3)]; c [See Warnings and Precautions (5.7)] dIf not otherwise specified in this table, consider avoiding concomitant use (see also information on medication-free intervals , use agent at the lowest appropriate dose, monitor for effects of the interaction, advise the patient to report potential effects, and be prepared to discontinue the agent and treat effects of the interaction
e [See Warnings and Precautions (5.5)]

7.2 Tyramine-Containing Foods and Beverages

PARNATE inhibits intestinal MAO, which is responsible for the catabolism of tyramine in food and beverages. As a result of this inhibition, large amounts of tyramine may enter the systemic circulation and precipitate a sudden elevation in blood pressure or hypertensive crisis [see Warnings and Precautions (5.2)]. Instruct PARNATE-treated patients to avoid foods and beverages with significant tyramine content during treatment with PARNATE or within 2 weeks of stopping treatment (see Table 5 for a list of food and beverages containing significant amounts of tyramine).

Table 5: Foods and Beverages with and without Significant Amounts of Tyramine

Class of Food or Beverage | Tyramine-Rich Foods and Beverages to Avoid | Acceptable Foods and Drinks, Containing No or Little Tyramine
Meat, Poultry, and Fish | Air dried, aged and fermented meats, sausages and salamis (including cacciatore, hard salami and mortadella); pickled herring; and any spoiled or improperly stored meat, poultry, and fish (e.g., foods that have undergone changes in coloration, odor, or become moldy); spoiled or improperly stored animal livers | Fresh meat, poultry, and fish, including fresh processed meats (e.g., lunch meats, hot dogs, breakfast sausage, and cooked sliced ham)
Vegetables | Broad bean pods (fava bean pods) | All other vegetables
Dairy | Aged cheeses | Processed cheeses, mozzarella, ricotta cheese, cottage cheese, and yogurt
Beverages | All varieties of tap beer and beers that have not been pasteurized so as to allow for ongoing fermentation and excessive amounts of caffeine. | Concomitant use of alcohol with PARNATE is not recommended. (Bottled and canned beers and wines contain little or no tyramine.)
Other | Concentrated yeast extract (e.g., Marmite), sauerkraut, most soybean products (including soy sauce and tofu), OTC supplements containing tyramine, and chocolate | Brewer’s yeast, baker’s yeast, soy milk, commercial chain restaurant pizzas prepared with cheeses low in tyramine

8 USE IN SPECIFIC POPULATIONS

8.1 Pregnancy

Risk Summary
There are limited published reports of placental infarction and congenital anomalies in association with use of PARNATE during pregnancy; however, these reports may not adequately inform the presence or absence of drug-associated risk with the use of PARNATE during pregnancy. In the U.S. general population, the background risk of major birth defects and miscarriage in clinically recognized pregnancies is 2-4% and 15-20%, respectively. Animal embryo-fetal development studies were not conducted with tranylcypromine; however, published animal reproduction studies report placental transfer of tranylcypromine in rats and a dose-dependent decrease in uterine blood flow in pregnant sheep. Advise pregnant women of the potential risk to a fetus.

Clinical Considerations
Labor or Delivery
During labor and delivery, the potential for interactions between PARNATE and drugs or procedures (e.g., epidural anesthesia) should be taken into account in women who have received PARNATE [see Warnings and Precautions (5.6) and Drug Interactions (7.1)].

8.2 Lactation

Risk Summary
Tranylcypromine is present in human milk. There is no available information on the effects of tranylcypromine on milk production. There is no available information on the effects of tranylcypromine on a breastfed child; however, because of the potential for serious adverse reactions in a breastfed infant, advise nursing women to discontinue breastfeeding during treatment with PARNATE

8.4 Pediatric Use

Safety and effectiveness of PARNATE in the pediatric population have not been established. All risks associated with the use of PARNATE, including the risk of suicidal thoughts and behavior, apply to adults and pediatric patients [see Boxed Warning and Warnings and Precautions (5)].

8.5 Geriatric Use

Older patients may be at greater risk of postural hypotension and other serious adverse reactions[see Warnings and Precautions (5)]. In general, dose selection for an elderly patient should be cautious, usually starting at the low end of the dosing range, reflecting the greater frequency of decreased hepatic, renal, or cardiac function, and of concomitant disease or other drug therapy.

9 DRUG ABUSE AND DEPENDENCE

9.2 Abuse

Abuse of PARNATE has been reported. Some of these patients had a history of previous substance abuse.

The potential for abuse and the increased risk of serious adverse reactions with higher doses should be taken into account when considering the use of PARNATE for patients at increased risk for substance abuse.

9.3 Dependence

Dependence, evidenced by precipitation of withdrawal effects following abrupt discontinuation of PARNATE has been reported. Reported withdrawal effects included delirium (even with low daily doses), restlessness, anxiety, confusion, hallucinations, headache, weakness, diarrhea, and/or rapid relapse into depression. Thrombocytopenia and liver enzyme increases have also been observed in association with PARNATE withdrawal from high doses [see Overdosage (10.1)]

Withdrawal effects have appeared within 1 to 3 days of discontinuation and have persisted for several weeks after discontinuation. The use of daily doses greater than recommended and longer duration of use appear to be associated with a higher risk of withdrawal effects.

Monitor for withdrawal effects for at least 1 week after discontinuation. Consider discontinuing PARNATE therapy by slow, gradual dose reduction [see Dosage and Administration (2.3)].

10 OVERDOSAGE

10.1 Overdosage Symptoms, Signs, and Laboratory Abnormalities

Overdose of PARNATE can cause the adverse reactions generally associated with PARNATE administration [see Warnings and Precautions (5), Adverse Reactions (6)and Drug Interactions (7.1)]. However, these reactions may be more severe, including fatal reactions. Effects reported with overdosage of PARNATE and/or other MAOIs include:

- Insomnia, restlessness, and anxiety, progressing in severe cases to agitation, mental confusion, and incoherence; delirium; seizures
- Hypotension, dizziness, weakness, and drowsiness, progressing in severe cases to extreme dizziness and shock
- Hypertension with severe headache and other symptoms/complications
- Twitching or myoclonic fibrillation of skeletal muscles, with hyperpyrexia, sometimes progressing to generalized rigidity and coma

10.2 Overdosage Management

There are no specific antidotes for PARNATE. For current information on the management of poisoning or overdosage, contact a poison control center at 1-800-222-1222.
Abrupt withdrawal of PARNATE following overdosage can precipitate withdrawal symptoms, including delirium [see Warnings and Precautions 5.9)and Drug Abuse and Dependence (9.3)].
Medical management should normally consist of general supportive measures, close observation of vital signs, and steps to counteract specific manifestations as they occur [see Warnings and Precautions (5)].The toxic effects of PARNATE may be delayed or prolonged following the last dose of the drug [see Clinical Pharmacology (12.2)]. Therefore, the patient should be closely observed for at least 1 week.

Data on the dialyzability of tranylcypromine are lacking.

11 DESCRIPTION

Tranylcypromine sulfate, the active ingredient of PARNATE, is a non-hydrazine MAOI. The chemical name is (±)‑trans‑2‑phenylcyclopropylamine sulfate (2:1). The molecular formula is (C9H11N)2•H2SO4 and its molecular weight is 364.46. The structural formula is:

PARNATE film-coated tablets are intended for oral administration. Each round, rose‑red tablet is debossed on one side with the product name “PARNATE” and “SB” and contains tranylcypromine sulfate equivalent to 10 mg of tranylcypromine.

Inactive ingredients consist of microcrystalline cellulose, anhydrous citric acid, croscarmellose sodium, D&C Red No. 7, FD&C Blue No. 2, FD&C Yellow No. 6, gelatin, lactose, magnesium stearate, talc, titanium dioxide, carnauba wax, polyethylene glycol 400 and 8000, and hypromellose.

12 CLINICAL PHARMACOLOGY

12.1 Mechanism of Action

The mechanism of action of PARNATE as an antidepressant is not fully understood, but is presumed to be linked to potentiation of monoamine neurotransmitter activity in the central nervous system (CNS) resulting from its irreversible inhibition of the enzyme monoamine oxidase (MAO).

12.2 Pharmacodynamics

Although tranylcypromine is eliminated in 24 hours, recovery MAO activity take up to 3 to 5 days [see Warnings and Precautions (5.9)].

13 NONCLINICAL TOXICOLOGY

13.1 Carcinogenesis, Mutagenesis, Impairment of Fertility

No carcinogenesis, mutagenesis, or fertility impairment studies were conducted.

16 HOW SUPPLIED/STORAGE AND HANDLING

PARNATE (tranylcypromine) tablets are available as:

- 10 mg: film-coated, round, rose-red and debossed with the product name “PARNATE” and “SB” on one side of the tablet containing tranylcypromine sulfate equivalent to 10 mg of tranylcypromine.
- Bottles of 100 tablets: NDC 59212-447-10

Store between 15° and 30°C (59° and 86°F). Dispense in a tight, light resistant container.

17 PATIENT COUNSELING INFORMATION

Advise the patient to read FDA-approved patient labeling (Medication Guide).

Suicidal Thoughts and Behaviors
Advise patients and caregivers to look for the emergence of suicidal thoughts and behaviors, especially early during treatment and when the dosage is adjusted up or down [see Box Warning and Warnings and Precautions (5.1)].
Hypertensive Crisis
Advise the patient on possible symptoms and instruct the patient to seek immediate medical attention if related signs or symptoms are present [see Boxed Warning and Warnings and Precautions (5.2)]
Serotonin Syndrome
Advise the patient on possible symptoms, and explain the potentially fatal nature of serotonin syndrome and that it may result from an interaction with other serotonergic drugs. Instruct the patient to seek immediate medical attention if related signs or symptoms are present [see Warnings and Precautions (5.3)]

Interaction with Other Drugs and Dietary Supplements[see Contraindications (4.1)and Drug Interactions (7.1)]

- Warn the patient not to take concomitant medications, whether prescription or over‑the‑counter drugs, or dietary supplements without prior consultation with a health care provider able to provide advice on the potential for interactions.
- Explain to the patient that some other drugs may require a medication-free interval even after discontinuation of PARNATE.
- Advise the patient to inform other physicians, pharmacists, and dentists about the treatment with PARNATE.

Interaction with Foods and Beverages [see Contraindications (4.1)and Drug Interactions (7.2)]

- Warn the patient to avoid tyramine-rich foods and beverages.
- Advise the patient to avoid eating foods if storage conditions or freshness is unknown and to be cautious of foods of unknown age or composition even if refrigerated.

Hypotension

Advise the patient to report any symptoms of hypotension in the initial phase of treatment to the healthcare provider, because occurrence of such symptoms may require discontinuation [see Dosage and Administration (2.1) and Warnings and Precautions (5.5)].

Withdrawal Symptoms

Warn the patient not to stop PARNATE treatment abruptly, as withdrawal symptoms may occur and that the effect of PARNATE may continue even after discontinuation [see Warnings and Precautions (5.8, 5.9)].

Aggravation of Coexisting Symptoms of Depression

Inform the patient that PARNATE may aggravate coexisting symptoms in depression, such as anxiety and agitation and instruct them to contact their healthcare provider if they experience such symptoms [see Warnings and Precautions (5.13)].

Effects on Ability to Drive or Use Machinery [see Warnings and Precautions (5.14)]

- Warn the patient about the possible adverse reactions that can impair the performance of potentially hazardous tasks such as driving a car or operating machinery.
- Tell the patient not to operate hazardous machinery and automobiles until they are reasonably certain that their ability to engage in such activities is not impaired.

PARNATE® is a registered trademark of Mercury Pharma Group Limited. Distributed by Advanz Pharma (US) Corp. under license.

Manufactured for:
Advanz Pharma (US) Corp.
Bannockburn, IL 60015

MEDICATION GUIDE

BOXED WARNING

MEDICATION GUIDE
PARNATE® (PAR-nate)
(tranylcypromine)
Tablets

What is the most important information I should know about PARNATE?
PARNATE can cause serious side effects including:

- Increase in suicidal thoughts or actions in some children, teenagers, and young adults within the first few months of treatment and when the PARNATE dose is changed. Depression and other serious mental illnesses are the most important causes of suicidal thoughts and actions. Some people may have a particularly high risk of having suicidal thoughts or actions.These include people who have, or have a family history of, bipolar illness (also called manic-depressive illness) or suicidal thoughts or actions. PARNATE is not for use in children.

How can I watch for and try to prevent suicidal thoughts and actions?

- Pay close attention to any changes, especially sudden changes, in mood, behaviors, thoughts, or feelings. This is very important when an antidepressant medicine is started or when the dose is changed.
- Call the healthcare provider right away to report new or sudden changes in mood, behavior, thoughts, or feelings.
- Keep all follow-up visits with your healthcare provider as scheduled. Call the healthcare provider between visits as needed, especially if you have concerns about symptoms

Call a healthcare provider right away if you have any of the following symptoms, especially if they are new, worse, or worry you:

- thoughts about suicide or dying

- attempts to commit suicide

- new or worse depression

- new or worse anxiety

- feeling agitated, restless, angry or irritable

- panic attacks

- trouble sleeping

- new or worse irritability

- acting aggressive, being angry or violent

- acting on dangerous impulses

- an extreme increase in activity or talking (mania)

- other unusual changes in behavior or mood

- A sudden, severe increase in blood pressure (hypertensive crisis). A hypertensive crisis can happen when you eat certain foods and drinks certain beverages during or after PARNATE treatment. A hypertensive crisis can lead to stroke and death. People who have thyroid problems (hyperthyroidism) may have a higher chance of having a hypertensive crisis. Symptoms of a hypertensive crisis may include:

- sudden, severe headache

- nausea

- vomiting

- stiff or sore neck

- a fast heartbeat (palpitations) or a change in the way your heart beats

- excessive sweating, sometimes with fever or cold, clammy skin

- the pupils in your eyes increase in size

- light bothers your eyes

- fast or slow heart beat with chest pain

- bleeding in your brain

A hypertensive crisis can also happen if you take PARNATE with certain other medicines. See, “Who should not take PARNATE?”
Avoid foods and drinks with a lot of tyramine while taking PARNATE and for 2 weeks after you stop taking it. For a list of some of the foods and drinks you should avoid during treatment with PARNATE see, “What should I avoid while taking PARNATE?”

BOXED WARNING

What is PARNATE?
PARNATE is a prescription medicine used to treat adults with a certain type of depression called major depressive disorder (MDD) who have not responded well to treatment with other medicines used to treat depression (antidepressants). PARNATE belongs to a class of medicines called monoamine oxidase inhibitors (MAOIs).

- It is important to talk with your healthcare provider about the risks of treating depression and the risk of not treating it. Talk with your healthcare provider about all your treatment choices.
- PARNATE is not for use as the first medicine to treat MDD.
- It is not known if PARNATE is safe and effective for use in children.

BOXED WARNING

Who should not take PARNATE?
Taking PARNATE with certain antidepressants and certain pain, allergy symptom, and cold and cough symptom medicines may cause a potentially life-threatening hypertensive crisis or a problem called serotonin syndrome. See, "What is the most important information I should know about PARNATE?” and “What are the possible side effects of PARNATE?”

BOXED WARNING

Do not take PARNATE if you:

- take certain medicines, including:
  - antidepressants, such as:
    - other monoamine oxidase inhibitors (MAOIs)
    - selective serotonin reuptake inhibitors (SSRIs) and serotonin and norepinephrine reuptake inhibitors (SNRIs)
    - tricyclic antidepressants
    - other antidepressants, such as amoxapine, bupropion, maprotiline, nefazodone, trazodone, vilazodone, vortioxetine
    - amphetamines and methylphenidates
  - medicines that can raise blood pressure (sympathomimetic medicine), such as pseudoephedrine, phenylephrine and ephedrine. These medicines are in some cold, hay fever or weight-loss medicines.
  - sympathomimetic herbal medicines or dietary supplements
  - antihistamines (allergy medicines)
  - triptans
  - buspirone
  - carbamazepine
  - dextromethorphan
  - dopamine
  - hydroxytryptophan and tryptophan
  - levodopa and methyldopa
  - meperidine
  - rasagline
  - resperine
  - s-adenosyl-L-methionine (SAM-e)
  - tapentadol
  - tetrabenazine

Ask your healthcare provider or pharmacist if you are not sure if you take any of these medicines.

- have a tumor on your adrenal gland called a pheochromocytoma or a type of tumor called a paraganglioma.

BOXED WARNING

Before taking PARNATE, tell your healthcare provider about all your medical conditions, including if you:

- have high or low blood pressure
- have heart problems
- have cerebrovascular problems or have had a stroke
- have headaches
- have, or have a family history of, bipolar disorder, mania, or hypomania
- plan to have surgery
- have liver or thyroid problems
- have or have had seizures or convulsions
- have diabetes
- are pregnant or plan to become pregnant. PARNATE may harm your unborn baby.
- are breastfeeding or plan to breastfeed. PARNATE passes into your breast milk. Do not breastfeed during treatment with PARNATE. Talk to your healthcare provider about the best way to feed your baby while taking PARNATE.

Tell your healthcare provider about all the medicines you take, including prescription and over-the-counter medicines, vitamins, and herbal supplements.
PARNATE and some other medicines may affect each other causing serious side effects. PARNATE may affect the way other medicines work, and other medicines may affect how PARNATE works.
Some medicines need to be stopped for a period of time before you can start taking PARNATE and for a period of time after you stop taking PARNATE.
Know the medicines you take. Keep a list of them to show your healthcare providers, pharmacist, and dentist when you get a new medicine.

BOXED WARNING

How should I take PARNATE?

- Take PARNATE exactly as your healthcare provider tells you to take it.
- Your healthcare provider may need to change your dose of PARNATE until it is the right dose for you.
- Do not stop taking PARNATE without first talking to your healthcare provider. Stopping PARNATE suddenly may cause withdrawal symptoms. See, “What are the possible side effects of PARNATE?”
- Tell your healthcare provider if you think your condition has gotten worse during treatment with PARNATE.
- If you take too much PARNATE (overdose) call your healthcare provider or poison control, or go to the nearest hospital emergency room right away.

BOXED WARNING

What should I avoid while taking PARNATE?

- Do not eat foods or have drinks that have high amounts of tyramine while taking PARNATE or for 2 weeks after you stop taking PARNATE.
  - All foods you eat should be fresh or properly frozen.
  - Avoid foods when you do not know how those foods should be stored.
  - Ask your healthcare provider if you are not sure if certain foods and drinks contain tyramine.

The table below lists some of the foods and drinks you should avoid while you take PARNATE.

Type of Food and Drink that contain Tyramine
Meat, Poultry, and Fish | - air dried, aged and fermented meats, sausages, and salamis - pickled herring - any spoiled or improperly stored meat, poultry, and fish. These foods have a change in color, odor, or are moldy. - spoiled or improperly stored animal livers
Vegetables | - broad bean pods (fava bean pods)
Dairy (milk products) | - aged cheeses
Drinks | - all tap beers and other beers that have not been pasteurized
Other | - concentrated yeast extract (such as Marmite) - most soybean products (including soy sauce and tofu) - sauerkraut - over-the-counter supplements containing tyramine

- Do not drive, operate heavy machinery, or do other dangerous activities until you know how PARNATE affects you.
- Do not drink alcohol while taking PARNATE.

BOXED WARNING

What are the possible side effects of PARNATE?

PARNATE may cause serious side effects, including:

- See “What is the most important information I should know about PARNATE?”
- Serotonin Syndrome. A potentially life-threatening problem called serotonin syndrome can happen when you take PARNATE with certain other medicines. See, "Who should not take PARNATE?" Symptoms of serotonin syndrome may include:
  - agitation, confusion
  - seeing or hearing things that are not real (hallucinations)
  - coma
  - rapid pulse
  - changes in blood pressure
  - dizziness
  - sweating
  - flushing
  - high body temperature (hyperthermia)
  - fever
  - seizures
  - tremors, stiff muscles, or muscle twitching
  - becoming unstable
  - nausea, vomiting, diarrhea
  If you have any of these symptoms, call your healthcare provider or go to the nearest hospital emergency room right away.
- Mania or hypomania (manic episodes) in people who have a history of bipolar disorder.
  - greatly increased energy
  - severe problems sleeping
  - racing thoughts
  - reckless behavior
  - unusually grand ideas
  - excessive happiness or irritability
  - talking more or faster than usual
- Low blood pressure (hypotension) including a drop in your blood pressure when you stand or sit up (postural hypotension). This can happen more often in people who have high blood pressure (hypertension) and when the PARNATE dose is changed. Postural hypotension may cause you to feel dizzy and faint (syncope).
- Changes in your blood pressure (hypotension or hypertension) during surgery and during the time around surgery (perioperative). Taking PARNATE with certain medicines used for anesthesia can cause hypotension or hypertension. If you plan to have surgery, tell your surgeon or the healthcare provider who will give you anesthesia that you take PARNATE. Your healthcare provider should stop PARNATE at least 10 days before you have surgery.

Withdrawal symptoms. Talk with your healthcare provider before you stop taking PARNATE. Symptoms of withdrawal may include

- dizziness

- nausea

- headache

- irritability and agitation

- problems sleeping

- diarrhea

- anxiety

- abnormal dreams

- sweating

- confusion

- electric shock sensation (paresthesia)

- tiredness

- changes in your mood

- hypomania

- ringing in your ears (tinnitus)

- seizures

- Liver problems
- Seizures (convulsions). Seizures have happened in people who take too much PARNATE.
- Low blood sugar (hypoglycemia). Hypoglycemia has happened in people with diabetes who take medicines to lower blood sugar. Talk with your healthcare provider about checking your blood sugar during treatment with PARNATE. Tell your healthcare provider if your blood sugar gets low.
- Worsening of symptoms that can happen with depression, such as anxiety and agitation.

- dry mouth

- dizziness

- problems sleeping

- feeling sleepy

- headache

- overexcitement

- constipation

- blurry vision

- shakiness (tremor)

These are not all the side effects of PARNATE.
Call your doctor for medical advice about side effects. You may report side effects to FDA at 1-800-FDA-1088.

BOXED WARNING

How do I store PARNATE?

- Store PARNATE between 59°F to 86°F (15°C to 30°C).
- Store PARNATE in a tight, light resistant container.

Keep PARNATE and all medicines out of the reach of children.

BOXED WARNING

General information about the safe and effective use of PARNATE.
Medicines are sometimes prescribed for purposes other than those listed in a Medication Guide. Do not take PARNATE for a condition for which it was not prescribed. Do not give PARNATE to other people, even if they have the same symptoms you have. It may harm them. You can ask your healthcare provider or pharmacist for information about PARNATE that is written for health professionals.

BOXED WARNING

What are the ingredients in PARNATE?
Active Ingredient: tranylcypromine sulfate
Inactive Ingredients: microcrystalline cellulose, anhydrous citric acid, croscarmellose sodium, D&C Red No. 7, FD&C Blue No. 2, FD&C Yellow No. 6, gelatin, lactose, magnesium stearate, talc, titanium dioxide, carnauba wax, polyethylene glycol 400 and 8000 and hypromellose

Manufactured for:
Advanz Pharma (US) Corp.
Bannockburn, IL 60015

For more information, contact Advanz Pharma (US) Corp. at 1-877-370-1142.

PARNATE® is a registered trademark of Mercury Pharma Group Limited. Distributed by Advanz Pharma (US) Corp. under license.

This Medication Guide has been approved by the U.S. Food and Drug Administration
Revised: 11/23

PRINCIPAL DISPLAY PANEL

Bottle Label

NDC 59212-447-10 100 Tablets

Parnate®
(tranylcypromine sulfate)
Tablets

10 mg Rx only

Federal Law requires dispensing of PARNATE® with the Medication Guide under this label.

ADVANZ PHARMA